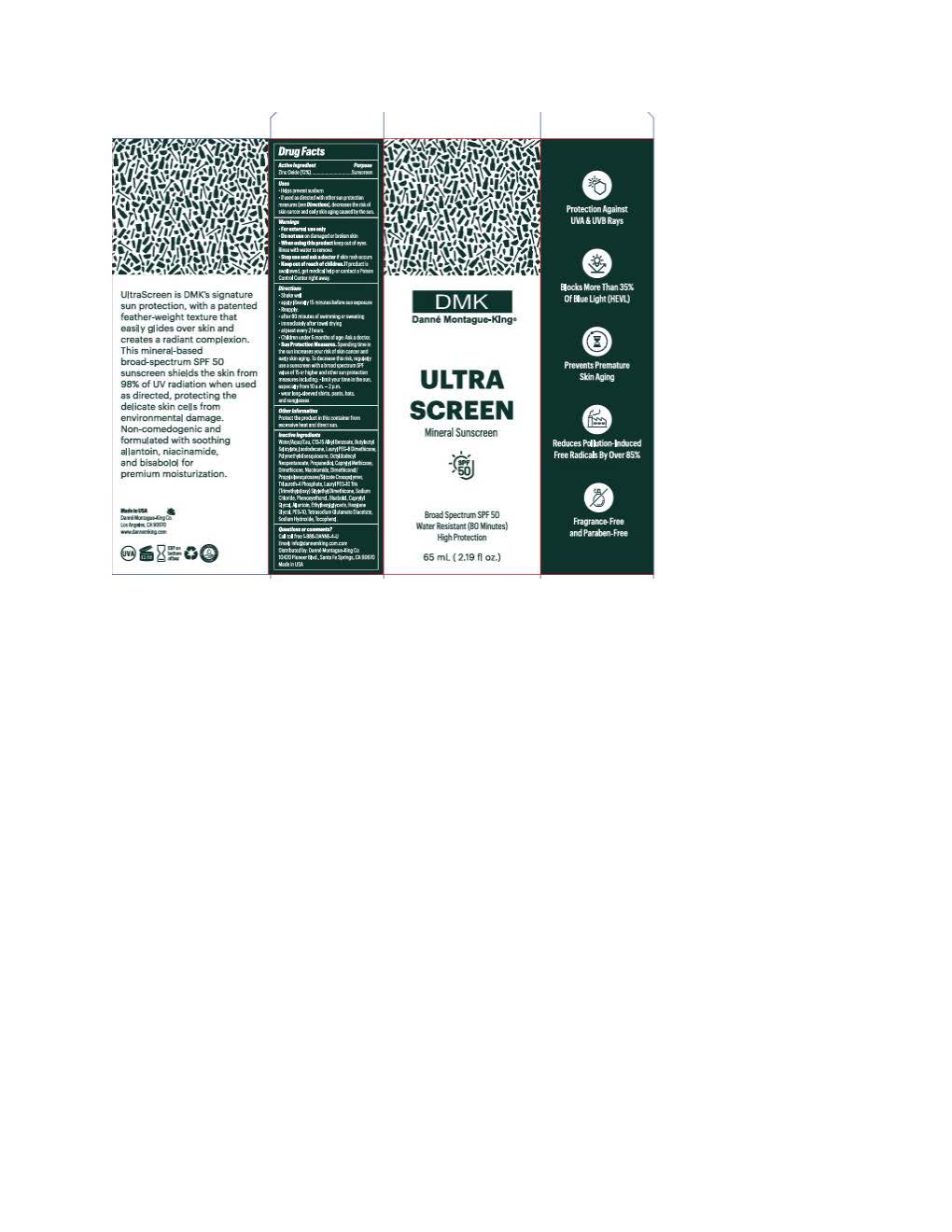 DRUG LABEL: DMK Ultrascreen Mineral Sunscreen
NDC: 81537-282 | Form: LOTION
Manufacturer: Danne Montague King
Category: otc | Type: HUMAN OTC DRUG LABEL
Date: 20260108

ACTIVE INGREDIENTS: ZINC OXIDE 132 mg/1 mL
INACTIVE INGREDIENTS: PALMITOYL TETRAPEPTIDE-7; TRILAURETH-4 PHOSPHATE; BUTYLOCTYL SALICYLATE; OCTYLDODECYL NEOPENTANOATE; ISODODECANE; .ALPHA.-BISABOLOL, (+)-; BUTYLENE GLYCOL; POLYSORBATE 20; SODIUM HYDROXIDE; WATER; NIACINAMIDE; ETHYLHEXYLGLYCERIN; HEXYLENE GLYCOL; GLYCERIN; DIMETHICONOL/PROPYLSILSESQUIOXANE/SILICATE CROSSPOLYMER (450000000 MW); PROPANEDIOL; TETRASODIUM GLUTAMATE DIACETATE; CARRAGEENAN; SODIUM CHLORIDE; PHENOXYETHANOL; PALMITOYL TRIPEPTIDE-1; .BETA.-TOCOPHEROL; POLYMETHYLSILSESQUIOXANE (4.5 MICRONS)

DMK Ultrascreen Mineral Sunscreen